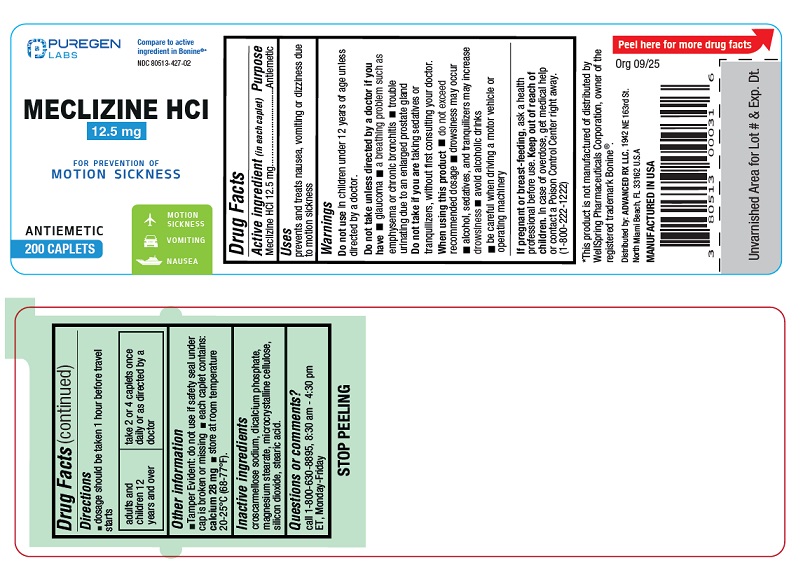 DRUG LABEL: MECLIZINE
NDC: 80513-427 | Form: TABLET
Manufacturer: Advanced Rx LLC
Category: otc | Type: HUMAN OTC DRUG LABEL
Date: 20250901

ACTIVE INGREDIENTS: MECLIZINE HYDROCHLORIDE 12.5 mg/1 1
INACTIVE INGREDIENTS: CROSCARMELLOSE SODIUM; CALCIUM PHOSPHATE, DIBASIC, ANHYDROUS; MAGNESIUM STEARATE; CELLULOSE, MICROCRYSTALLINE; SILICON DIOXIDE; STEARIC ACID

Active ingredient (in each caplet)

Meclizine HCl 12.5mg

Purpose

Antiemetic

Uses

prevents and treats nausea, vomiting or dizziness associated with motion sickness

Warnings

Do not usein children under 12 years of age unless directed by a doctor.

Do not take unless directed by a doctor if you have

- glaucoma
- a breathing problem such as emphysema or chronic bronchitis
- trouble urinating due to an enlarged prostate gland

Do not take if you aretaking sedatives or tranquilizers, without first consulting your doctor.

When using this product

- do not exceed recommended dosage
- drowsiness may occur
- alcohol, sedatives, and tranquilizers may increase drowsiness
- avoid alcoholic drinks
- be careful when driving a motor vehicle or operating machinery

If pregnant or breast-feeding,

ask a health professional before use.

Keep out of reach of children.

In case of overdose, get medical help or contact a Poison Control Center right away (1-800-222-1222).

Directions

- dosage should be taken 1 hour before travel starts

adults and children 12 years and over | take 2 or 4 caplets once daily or as directed by a doctor

Other information

- Tamper Evident: do not use if safety seal under cap is broken or missing
- each caplet contains: calcium 28 mg
- store at room temperature 20°-25°C (68°-77°F).

Inactive ingredients

croscarmellose sodium, dicalcium phosphate, magnesium stearate, microcrystalline cellulose, silicon dioxide, stearic acid.

Questions or comments?

call 1-800-630-8895, 8:30 am - 4:30 pm ET, Monday-Friday